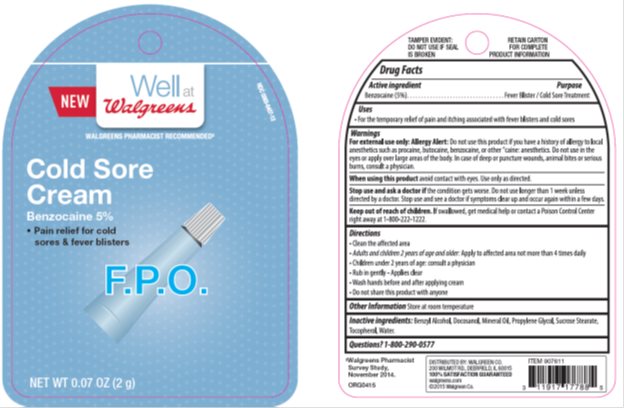 DRUG LABEL: Walgreens Cold Sore Treatment
NDC: 0363-3191 | Form: OINTMENT
Manufacturer: Walgreens
Category: otc | Type: HUMAN OTC DRUG LABEL
Date: 20150401

ACTIVE INGREDIENTS: BENZOCAINE 5.00 mg/1 g
INACTIVE INGREDIENTS: LIGHT MINERAL OIL 2.00 mg/1 g; DOCOSANOL 10 mg/1 g; BENZYL ALCOHOL 9.00 mg/1 g; SUCROSE STEARATE 5.00 mg/1 g; PROPYLENE GLYCOL 4.99 mg/1 g; WATER 64 mg/1 g

Drug Facts

Active ingredient

Benzocaine

Purpose

Cold Sore/Fever Blister Treatment/Pain Reliever

Keep Out of Reach of Children

If swallowed, get medical help or contact a Poison Control Center right away at 1-800-222-1222.

Uses

For treatment of cold sores/fever blisters on the face and lips

Warnings

For external use only: Allergy Alert: Do not use this product if you have a history of allergy to local anesthetics such as procaine, butocaine, benzocaine, or other “caine: anesthetics.

Do not use in the eyes or apply over large areas of the body. In case of deep or puncture wounds, animal bites or serious burns, consult a physician.

When using this product avoid contact with eyes. Use only as directed.

Stop use and ask a doctor if the condition gets worse. Do not use longer than 1 week unless directed by a doctor.

Directions

Clean the affected

Adults and children 2 years of age and older: Apply to affected area not more than 4 times daily

Children under 2 years of age: consult a physician

Rub in gently – Applies clear

Wash hands before and after applying cream

Do not share this product with anyone

Inactive Ingredients

Benzyl Alcohol, Docosanol, Mineral Oil, Propylene Glycol, Sucrose Stearate, Tocopherol, Water.